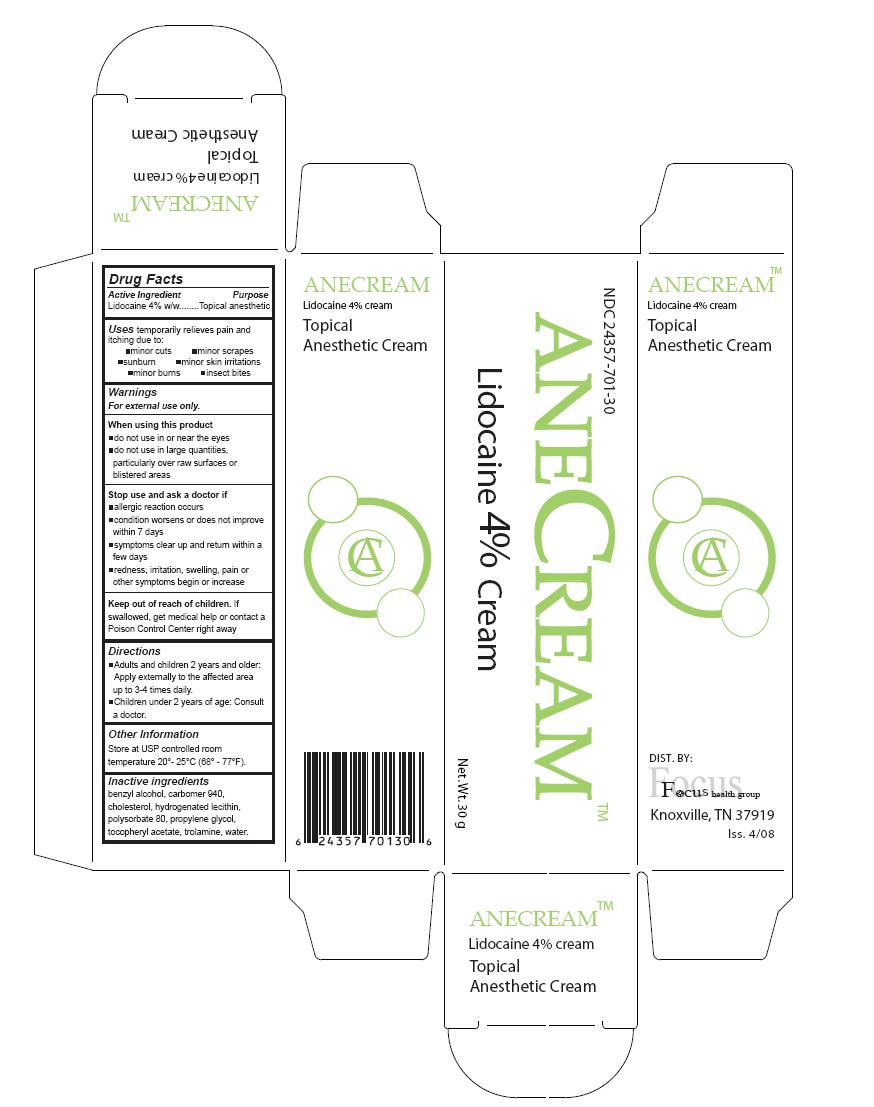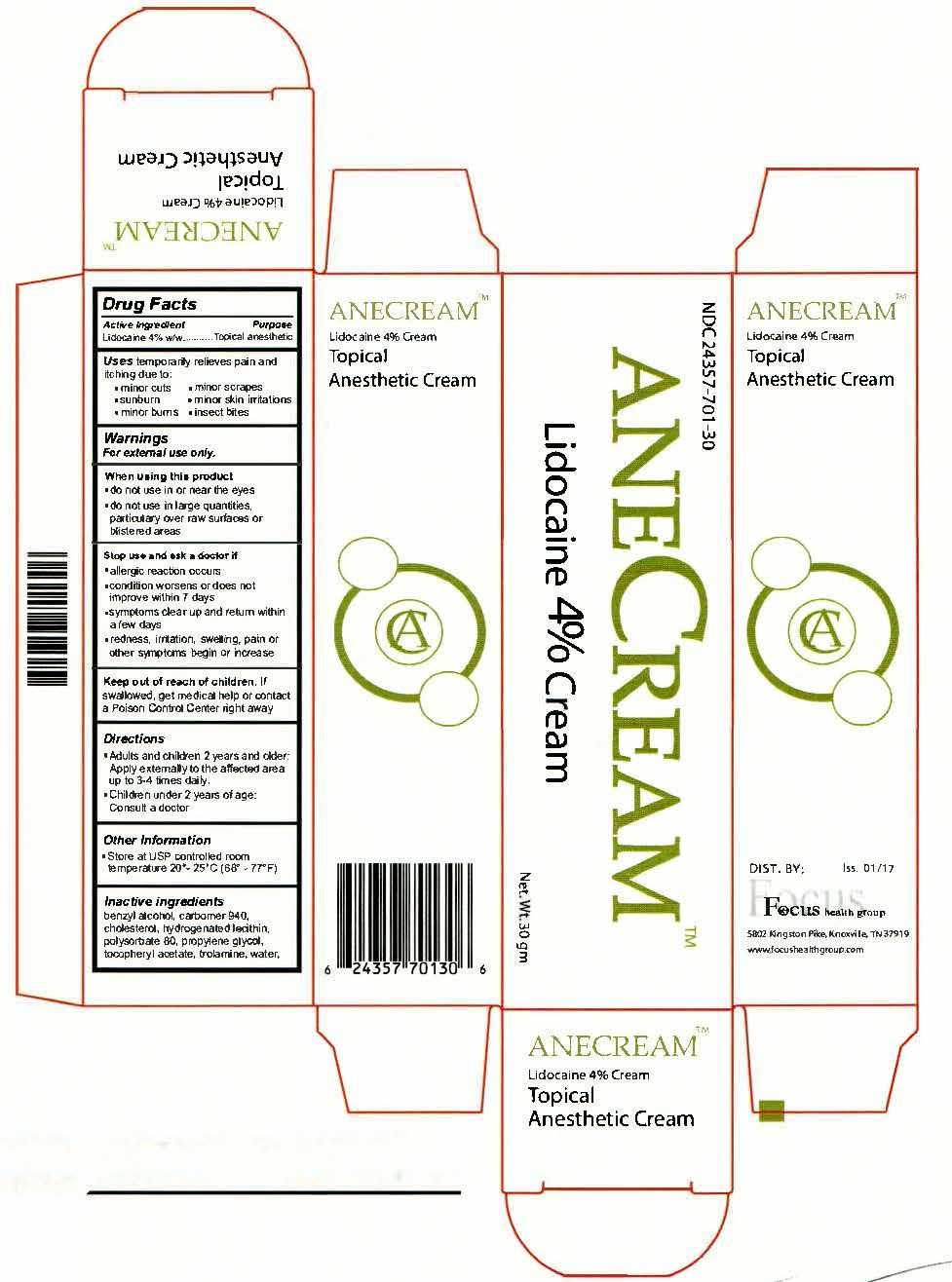 DRUG LABEL: Anecream
NDC: 24357-701 | Form: CREAM
Manufacturer: Focus Health Group
Category: otc | Type: HUMAN OTC DRUG LABEL
Date: 20250115

ACTIVE INGREDIENTS: LIDOCAINE 4 g/100 g
INACTIVE INGREDIENTS: BENZYL ALCOHOL; WATER; CARBOMER HOMOPOLYMER TYPE C; CHOLESTEROL; LECITHIN, SOYBEAN; POLYSORBATE 80; PROPYLENE GLYCOL; .ALPHA.-TOCOPHEROL ACETATE, DL-; TROLAMINE

Anecream 4%

Active Ingredient:

Lidocaine 4% w/w

Purpose

Topical anesthetic

Uses

temporarily relieves pain and itching due to:

- minor cuts
- minor scrapes
- sunburn
- minor skin irritations
- minor burns
- insect bites

WARNINGS

For external use only.

When using this product

- do not use in or near the eyes
- do not use in large quantities, particularly over raw surfaces or blistered areas

Stop use and ask doctor if

- Allergic reaction occurs
- condition worsens or does not improve within 7 days
- symptoms clear up and return within a few days
- redness, irritation, swelling, pain or other symptoms begin or increase

Keep out of reach of children.

If swallowed, get medical help or contact a Poison Control Center right away

Directions

- Adults and children 2 years and older: Apply externally to the affected area up to 3-4 times daily.
- Children under 2 years of age: Consult a doctor.

Other Information

Store at USP controlled room temperature 20-25 degC (68-77 deg.F).

Inactive ingredients

benzyl alcohol, carbomer 940, cholesterol, hydrogenated lecithin, polysorbate 80, propylene glycol, tocopherol acetate, trolamine, water

Anecream 30g Tube

The product package shown represents a sample of that currently in use. Additional packaging may also be available.

Anecream Topical Anesthetic Cream

Net. Wt. 30g

Distributed by: Focus Health Group

Knoxville, TN 37919